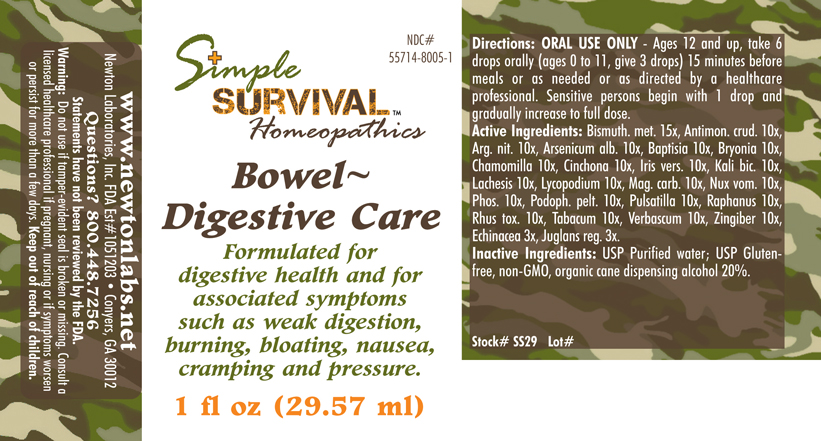 DRUG LABEL: Bowel - Digestive Care 
NDC: 55714-8005 | Form: LIQUID
Manufacturer: Newton Laboratories, Inc.
Category: homeopathic | Type: HUMAN OTC DRUG LABEL
Date: 20140415

ACTIVE INGREDIENTS: Bismuth 15 [hp_X]/1 mL; Antimony Trisulfide 10 [hp_X]/1 mL; Silver Nitrate 10 [hp_X]/1 mL; Arsenic Trioxide 10 [hp_X]/1 mL; Baptisia Tinctoria 10 [hp_X]/1 mL; Bryonia Alba Root 10 [hp_X]/1 mL; Matricaria Recutita 10 [hp_X]/1 mL; Cinchona Officinalis Bark 10 [hp_X]/1 mL; Iris Versicolor Root 10 [hp_X]/1 mL; Potassium Dichromate 10 [hp_X]/1 mL; Lachesis Muta Venom 10 [hp_X]/1 mL; Lycopodium Clavatum Spore 10 [hp_X]/1 mL; Magnesium Carbonate 10 [hp_X]/1 mL; Strychnos Nux-vomica Seed 10 [hp_M]/1 mL; Phosphorus 10 [hp_X]/1 mL; Podophyllum 10 [hp_X]/1 mL; Pulsatilla Vulgaris 10 [hp_X]/1 mL; Radish 10 [hp_X]/1 mL; Toxicodendron Pubescens Leaf 10 [hp_X]/1 mL; Tobacco Leaf 10 [hp_X]/1 mL; Verbascum Thapsus 10 [hp_X]/1 mL; Ginger 10 [hp_X]/1 mL; Echinacea, Unspecified 3 [hp_X]/1 mL; English Walnut 3 [hp_X]/1 mL
INACTIVE INGREDIENTS: Alcohol

Bowel - Digestive Care

INDICATIONS & USAGE SECTION

Bowel - Digestive Care Formulated for digestive health and for associated symptoms such as weak digestion, burning, bloating, nausea, cramping and pressure.

DOSAGE & ADMINISTRATION SECTION

Directions: ORAL USE ONLY - Ages 12 and up, take 6 drops orally (ages 0 to 11, give 3 drops) 15 minutes before meals or as needed or as directed by a healthcare professional. Sensitive persons begin with 1 drop and gradually increase to full dose.

OTC - ACTIVE INGREDIENT SECTION

Bismuthum met. 15x, Antimon.crud. 10x, Arg. nit. 10x, Arsenicum alb. 10x, Baptisia 10x, Bryonia 10x, Chamomilla 10x, Cinchona 10x, Iris vers. 10x, Kali bic. 10x, Lachesis 10x, Lycopodium 10x, Mag. carb. 10x, Nux vom. 10x, Phos. 10x, Podoph. pelt. 10x, Pulsatilla 10x, Raphanus 10x, Rhus tox. 10x, Tabacum 10x, Verbascum 10x, Zingiber 10x, Echinacea 3x, Juglans reg. 3x.

OTC - PURPOSE SECTION

Formulated for digestive health and for associated symptoms such as weak digestion, burning, bloating, nausea, cramping and pressure.

INACTIVE INGREDIENT SECTION

Inactive Ingredients: USP Purified Water; USP Gluten-free, non-GMO, organic cane dispensing alcohol 20%.

QUESTIONS SECTION

www.newtonlabs.net Newton Laboratories, Inc. FDA Est # 1051203 - Conyers, GA 30012
Questions? 1.800.448.7256

WARNINGS SECTION

Warning: Do not use if tamper - evident seal is broken or missing. Consult a licensed healthcare professional if pregnant, nursing or if symptoms worsen or persist for more than a few days. Keep out of reach of children

OTC - PREGNANCY OR BREAST FEEDING SECTION

Consult a licensed healthcare professional if pregnant, nursing or if symptoms worsen or persist for more than a few days.

OTC - KEEP OUT OF REACH OF CHILDREN SECTION

Keep out of reach of children.